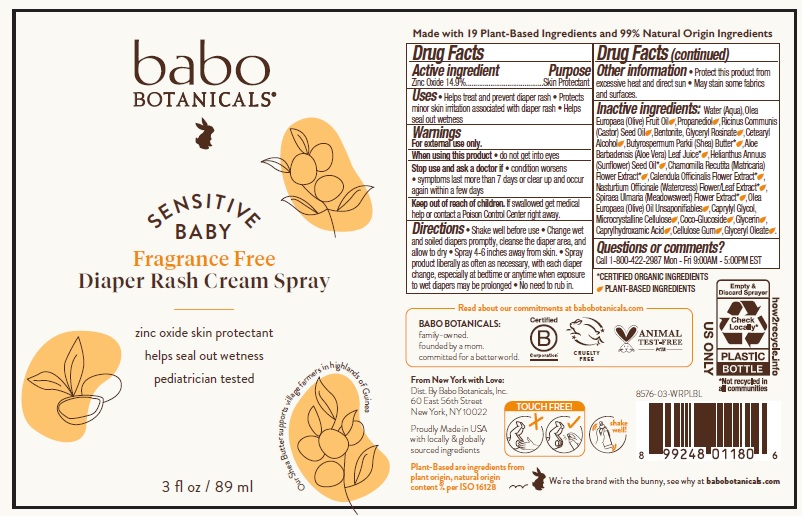 DRUG LABEL: Babo Botanicals Sensitive Baby Fragrance Free Diaper Rash
NDC: 79265-8576 | Form: SPRAY
Manufacturer: Babo Botanicals, Inc.
Category: otc | Type: HUMAN OTC DRUG LABEL
Date: 20231023

ACTIVE INGREDIENTS: ZINC OXIDE 206 mg/1 mL
INACTIVE INGREDIENTS: CELLULOSE, MICROCRYSTALLINE; ALOE VERA LEAF; OLIVE OIL; CASTOR OIL; GLYCERIN; CAPRYLHYDROXAMIC ACID; PROPANEDIOL; GLYCERYL ROSINATE; BENTONITE; NASTURTIUM OFFICINALE FLOWERING TOP; CALENDULA OFFICINALIS FLOWER; CETOSTEARYL ALCOHOL; CHAMOMILE; SHEA BUTTER; SUNFLOWER OIL; FILIPENDULA ULMARIA FLOWER; CAPRYLYL GLYCOL; OLEA EUROPAEA (OLIVE) OIL UNSAPONIFIABLES; CARBOXYMETHYLCELLULOSE SODIUM, UNSPECIFIED; WATER; GLYCERYL OLEATE; COCO GLUCOSIDE

Babo Botanicals Sensitive Baby Fragrance Free Diaper Rash Cream Spray

Active ingredient

Zinc Oxide 14.9%

Purpose

Skin Protectant

Uses

- Helps treat and prevent diaper rash
- Protects minor skin irritation associated with diaper rash
- Helps seal out wetness

Warnings

For external use only

When using this product

do not get into eyes

Stop use and ask a doctor if

- condition worsens
- symptoms last more than 7 days or clear up and occurs again within a few days.

Keep out of reach of children.

If swallowed get medical help or contact a Poison Control Center right away.

Directions

- Shake well before use
- Change wet and soiled diapers promptly, cleanse the diaper area, and allow to dry
- Spray 4-6 inches away from skin.
- Spray product liberally as often as necessary, with each diaper change, especially at bedtime or anytime when exposure to wet diapers may be prolonged
- No need to rub in.

Other information

- Protect this product from excessive heat and direct sun. May stain some fabrics and surfaces.

Inactive ingredients

Water (Aqua), Olea Europaea (Olive) Fruit Oil, Propanediol, Ricinus Communis (Castor) Seed Oil, Bentonite, Glyceryl Rosinate, Cetearyl Alcohol, Butyrospermum Parkii (Shea) Butter*, Aloe Barbadensis (Aloe Vera) Leaf Juice*, Helianthus Annuus (Sunflower) Seed Oil*, Chamomilla Recutita (Matricaria) Flower Extract*, Calendula Officinalis Flower Extract*, Nasturtium Officinale (Watercress) Flower/Leaf Extract*, Spiraea Ulmaria (Meadowsweet) Flower Extract*, Olea Europaea (Olive) Oil Unsaponifiables, Caprylyl Glycol, Microcrystalline Cellulose, Coco-Glucoside, Glycerin, Caprylhydroxamic Acid, Cellulose Gum, Glyceryl Oleate.

*Certified Organic Ingredients

Questions or comments?

Call 1-800-422-2987 Mon-Fri 9:00AM - 5:00PM EST

Company Information

Dist by Babo Botanicals, Inc.

60 East 56th Street New York, NY 10022